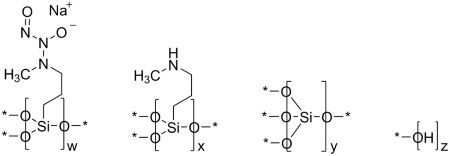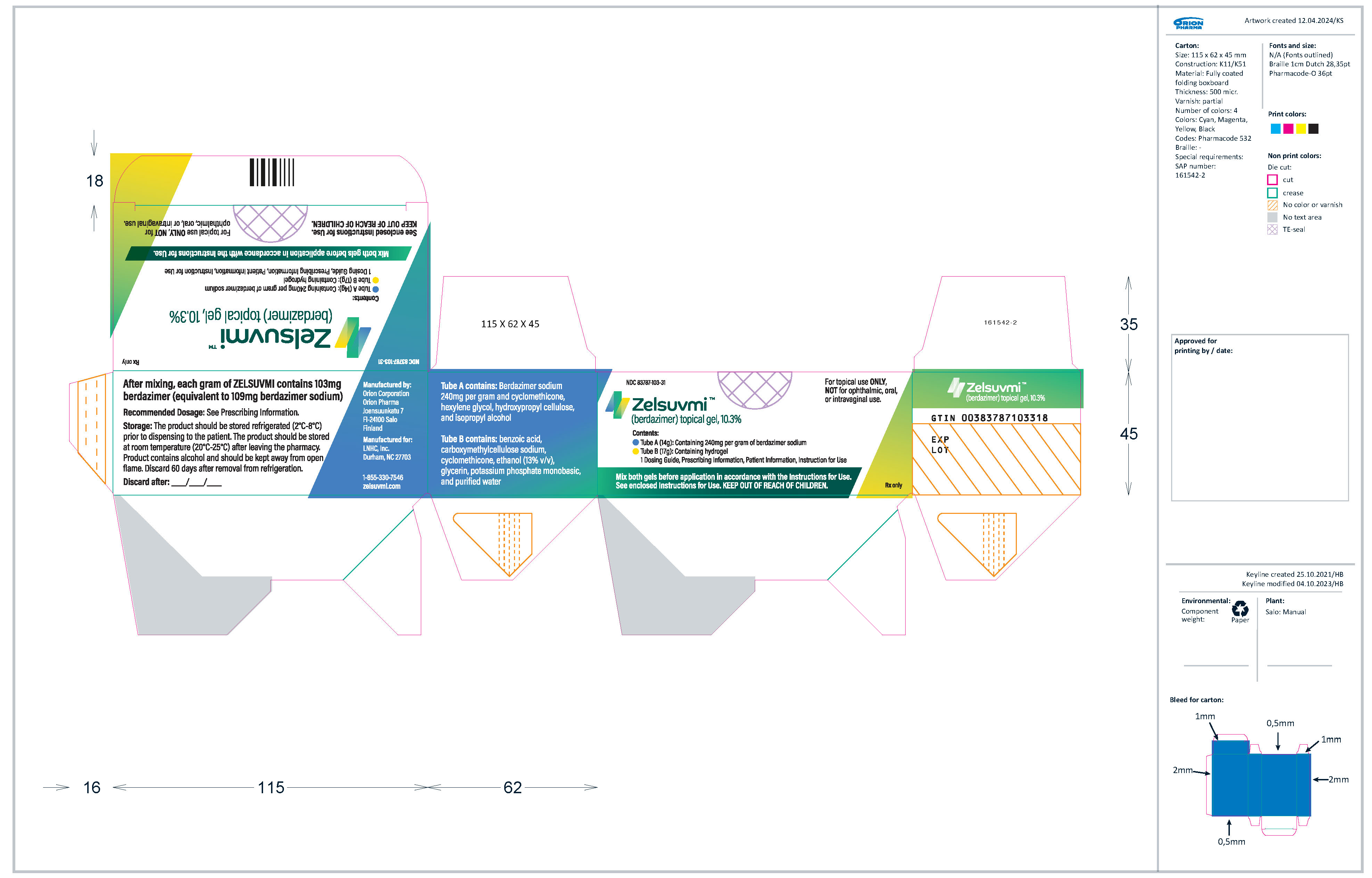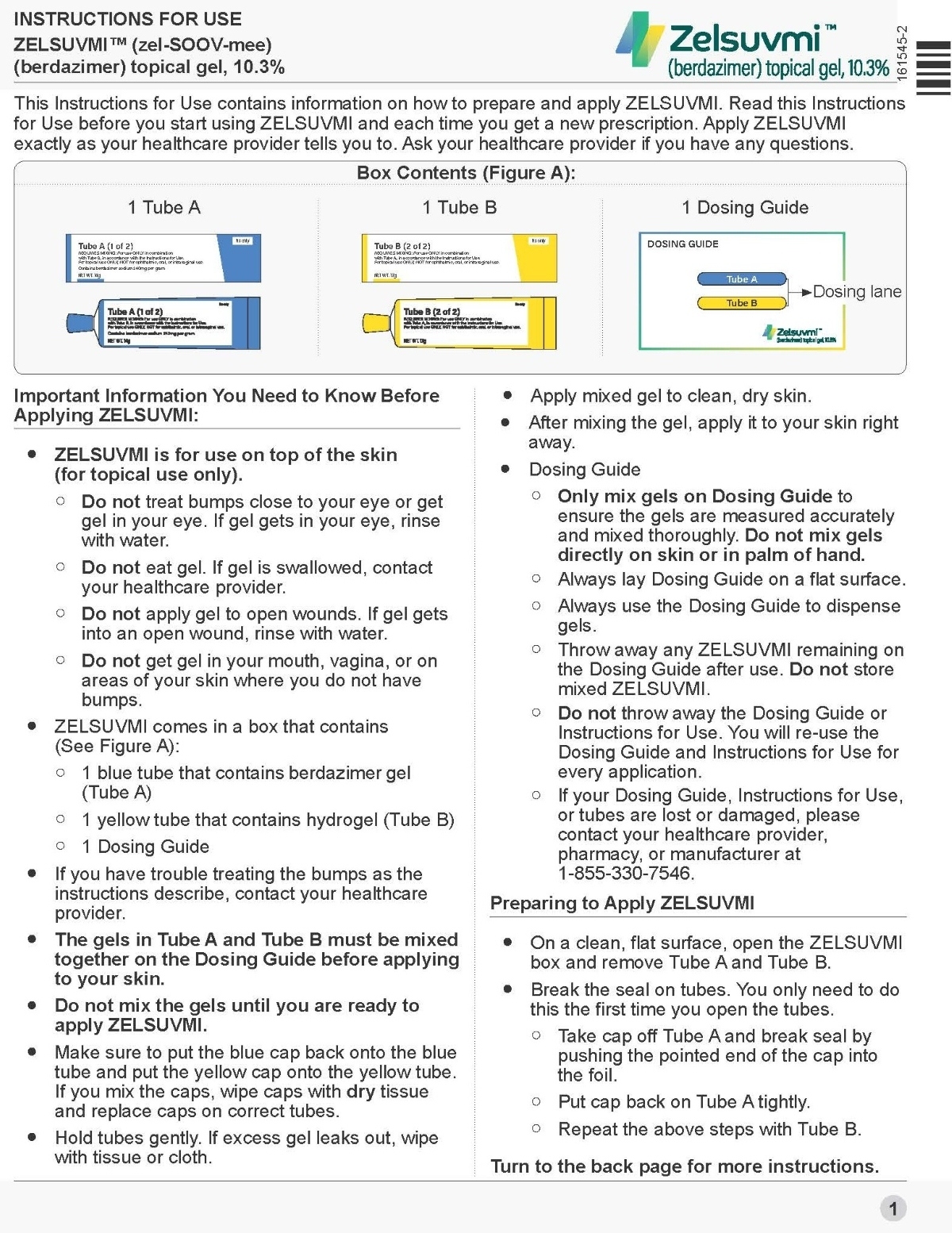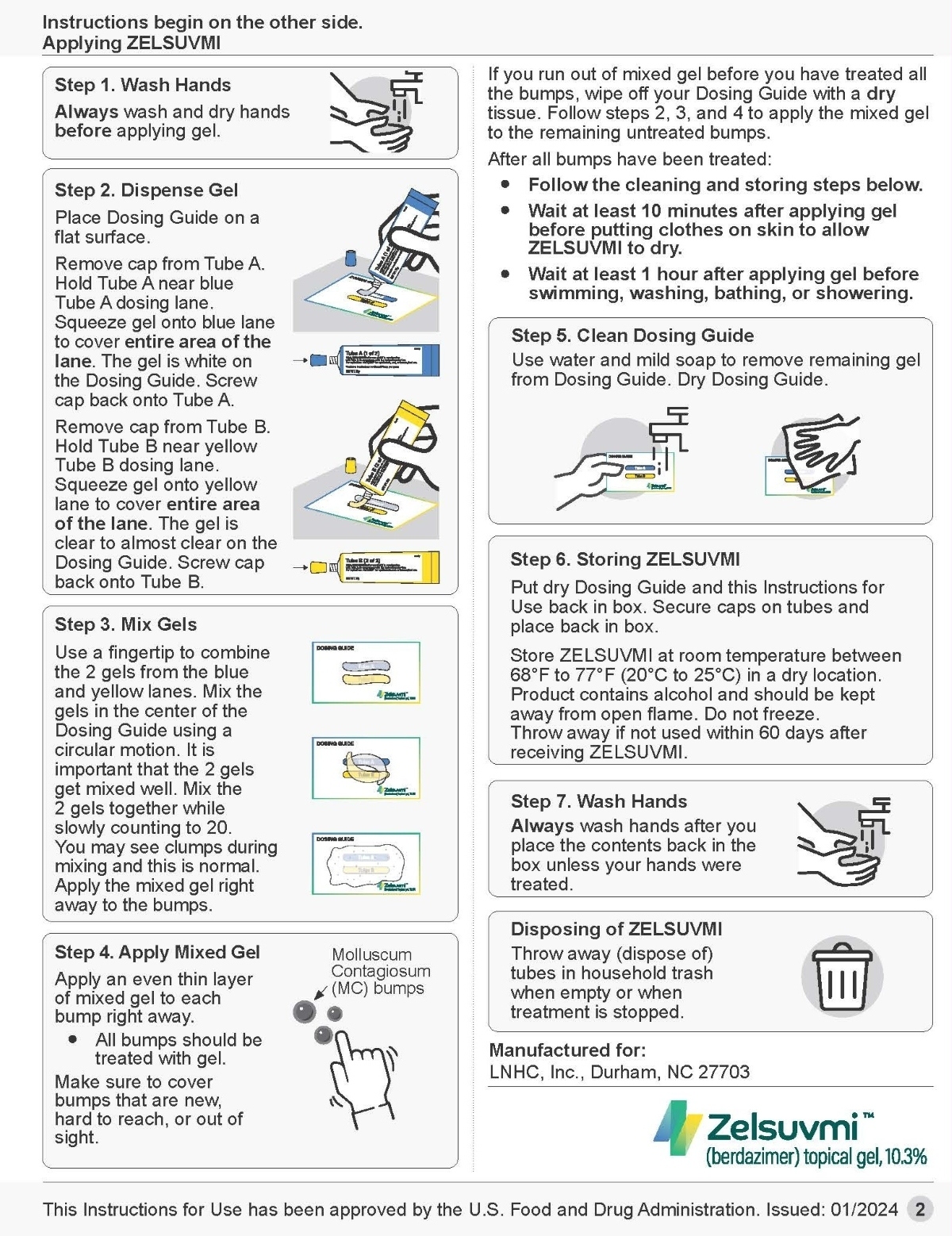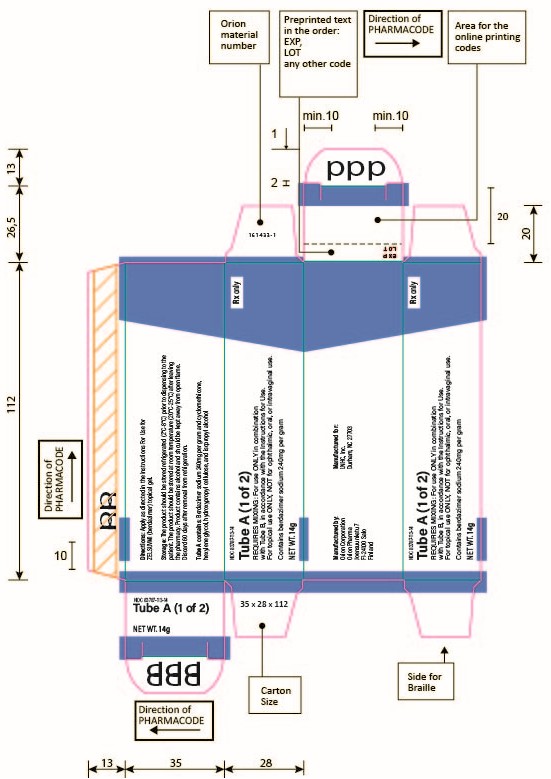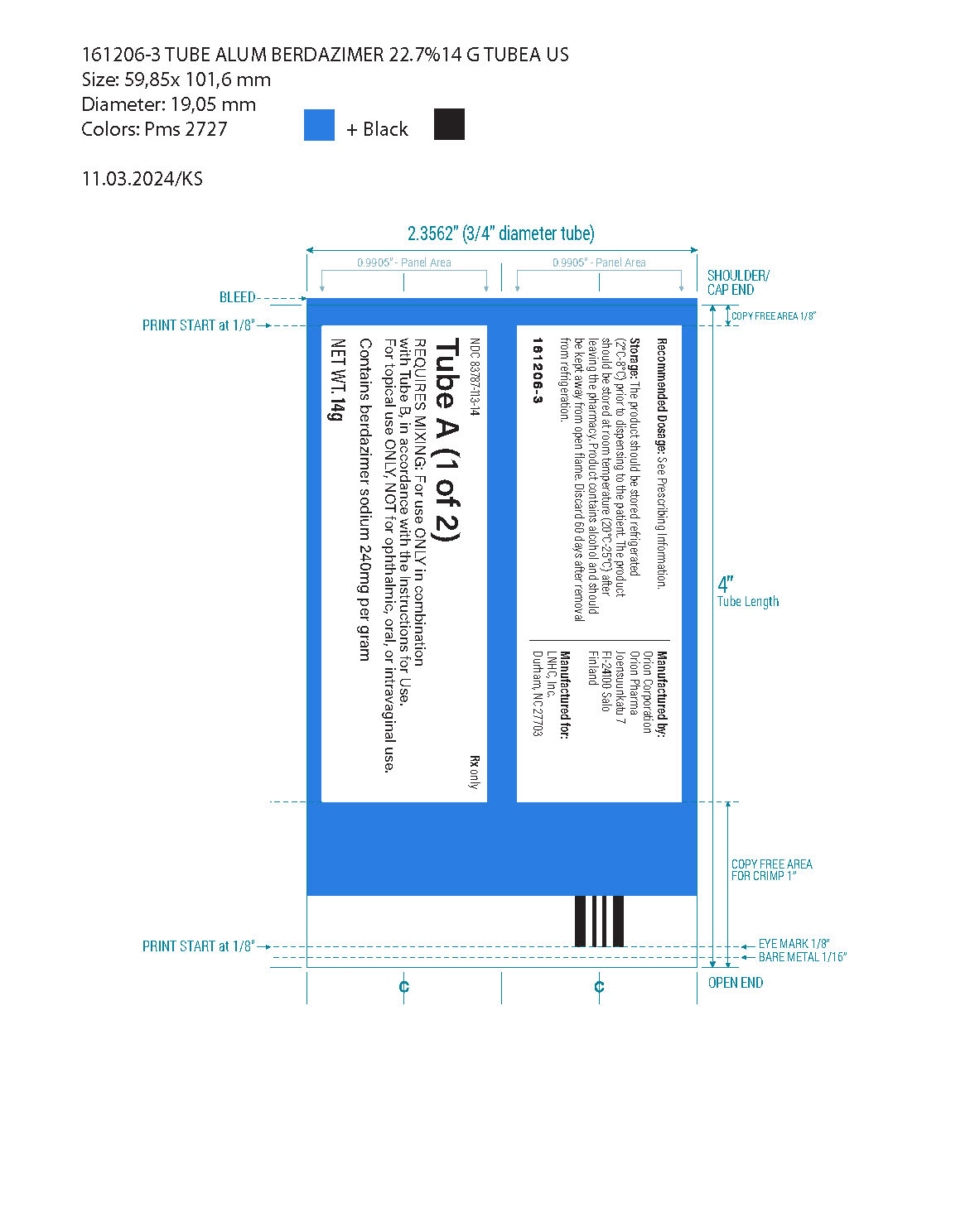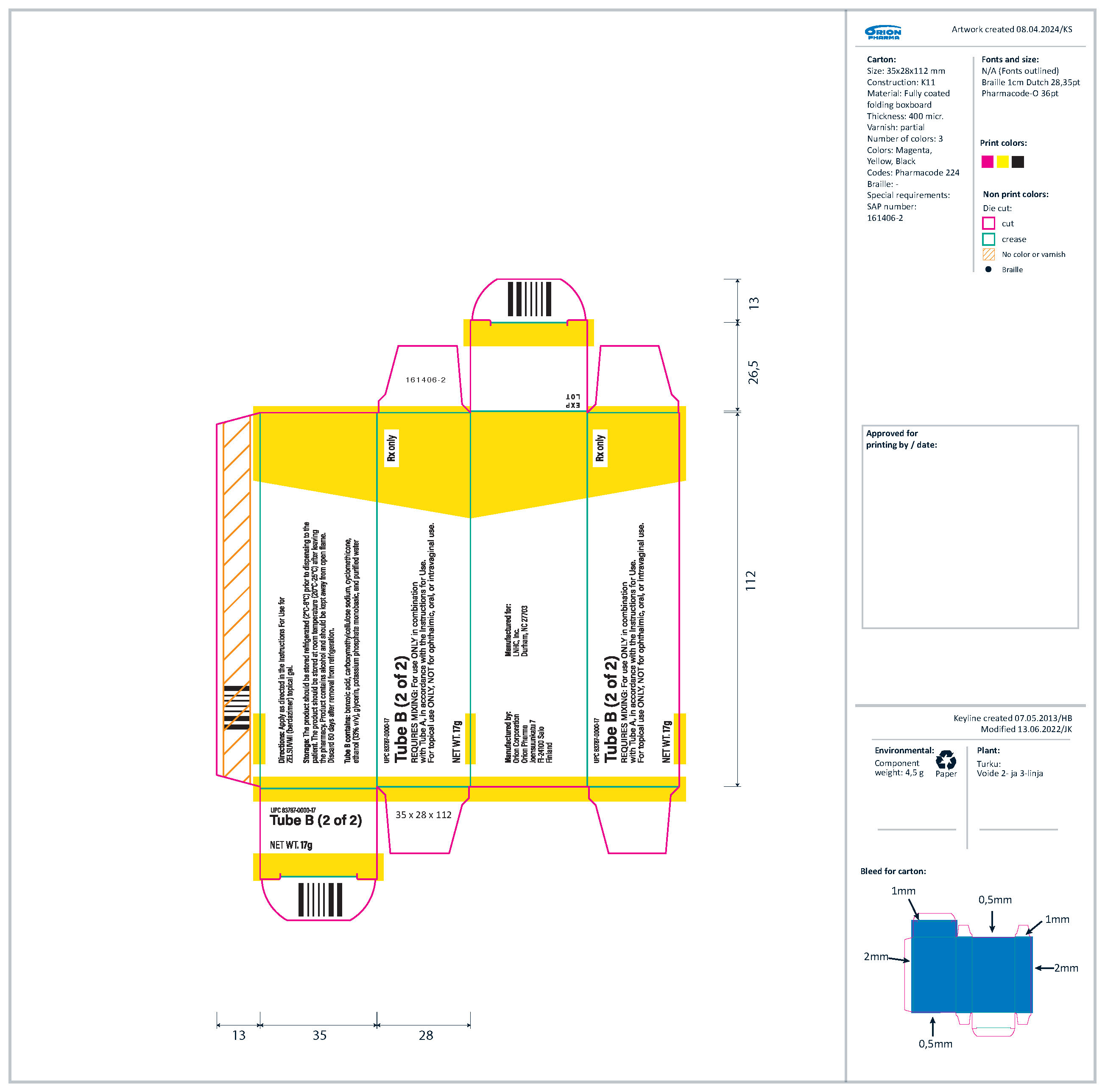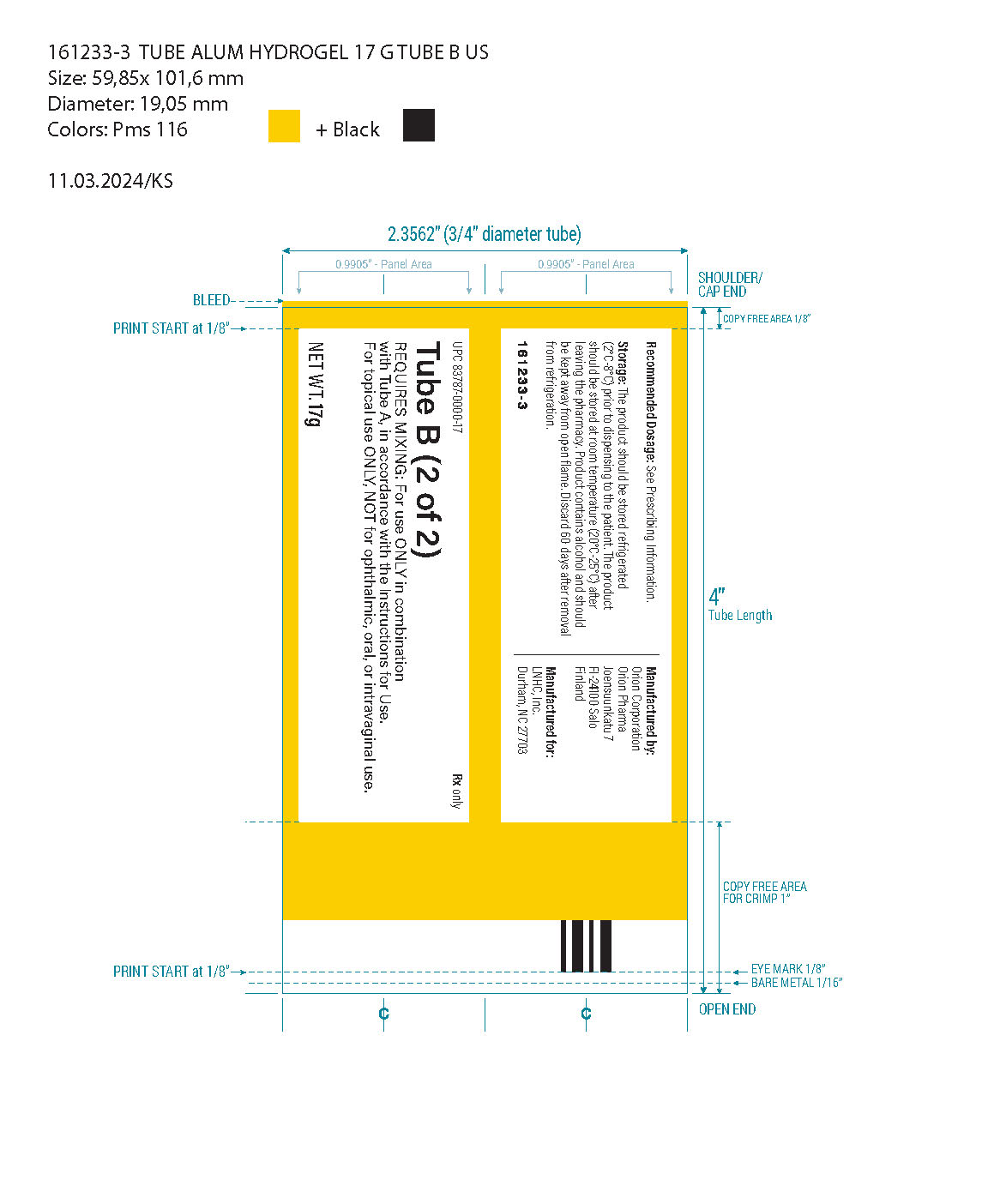 DRUG LABEL: ZELSUVMI
NDC: 83787-103 | Form: KIT | Route: TOPICAL
Manufacturer: LNHC, Inc.
Category: prescription | Type: HUMAN PRESCRIPTION DRUG LABEL
Date: 20250708

ACTIVE INGREDIENTS: BERDAZIMER SODIUM 240 mg/1 g

HIGHLIGHTS OF PRESCRIBING INFORMATION

These highlights do not include all the information needed to use ZELSUVMI safely and effectively. See full prescribing information for ZELSUVMI.
ZELSUVMI™ (berdazimer) topical gel
Initial U.S. Approval: 2024

1 INDICATIONS AND USAGE

ZELSUVMI™ is a nitric oxide (NO) releasing agent indicated for the topical treatment of molluscum contagiosum (MC) in adults and pediatric patients 1 year of age and older. (1)

2 DOSAGE AND ADMINISTRATION

- Dispense equal amounts from Tube A and Tube B per the dosing guide. (2.2)
- Mix together and immediately apply a thin layer of ZELSUVMI. (2.2)
- Apply once daily to each MC lesion for up to 12 weeks. (2.2)
- For topical use only and not for ophthalmic, oral, or intravaginal use. (2.2)

3 DOSAGE FORMS AND STRENGTHS

Topical gel: 10.3% berdazimer supplied as two tubes. Tube A contains berdazimer gel and Tube B contains hydrogel. (3)

4 CONTRAINDICATIONS

None.

5 WARNINGS AND PRECAUTIONS

Application Site Reactions: Application site reactions, including allergic contact dermatitis, occurred. Discontinue ZELSUVMI and initiate appropriate therapy. (5.1)

6 ADVERSE REACTIONS

The most commonly reported adverse reactions (≥1%) are application site reactions, including pain (such as burning or stinging sensations, 18.7%), erythema (11.7%), pruritus (5.7%), exfoliation (5.0%), dermatitis (4.9%), swelling (3.5%), erosion (1.6%), discoloration (1.5%), vesicles (1.5%), irritation (1.2%), and infection (1.1%). (6.1)

To report SUSPECTED ADVERSE REACTIONS, contact LNHC, Inc. at 1-855-330-7546 or FDA at 1-800-FDA-1088 or www.fda.gov/medwatch.

FULL PRESCRIBING INFORMATION

1 INDICATIONS AND USAGE

ZELSUVMI™ is indicated for the topical treatment of molluscum contagiosum (MC) in adults and pediatric patients 1 year of age and older.

2 DOSAGE AND ADMINISTRATION

2.1 Important Preparation and Administration Instructions

- ZELSUVMI is supplied in a carton containing the following:
  - Tube A containing berdazimer gel
  - Tube B containing hydrogel
  - Dosing guide
- Mix together equal amounts of gel from Tube A and Tube B before application [see Dosage and Administration (2.2)].
- Do not premix or store mixed ZELSUVMI.
- Instruct the patient to refer to the ZELSUVMI “Instructions for Use” for detailed instructions on the preparation and administration of ZELSUVMI [see Instructions for Use].

2.2 Recommended Dosage and Administration

- Dispense equal amounts (0.5 mL) of gel from Tube A and Tube B on the dosing guide. Immediately put the caps back on Tube A and Tube B tightly.
- Mix together on the dosing guide.
- Immediately apply ZELSUVMI as an even thin layer. Apply ZELSUVMI once daily to each MC lesion for up to 12 weeks.
- Wash hands after applying ZELSUVMI, unless hands are being treated.
- Allow ZELSUVMI to dry for 10 minutes after application.
- Avoid application to uninvolved skin and avoid transfer of applied ZELSUVMI to other areas, including the eye.
- Avoid swimming, bathing, or washing for 1 hour after application of ZELSUVMI.
- ZELSUVMI is for topical use only and not for ophthalmic, oral, or intravaginal use.

3 DOSAGE FORMS AND STRENGTHS

Topical gel: 10.3% berdazimer in an opaque white to off-white gel. ZELSUVMI is supplied as two tubes. Tube A with a blue label contains 14 grams of berdazimer gel and Tube B with a yellow label contains 17 grams of hydrogel.

4 CONTRAINDICATIONS

None.

5 WARNINGS AND PRECAUTIONS

5.1 Application Site Reactions

Application site reactions, including allergic contact dermatitis, have occurred in patients treated with ZELSUVMI. Suspect allergic contact dermatitis in the event of pain, pruritus, swelling or erythema at the application site lasting longer than 24 hours. If allergic contact dermatitis occurs, discontinue ZELSUVMI and initiate appropriate therapy.

6 ADVERSE REACTIONS

6.1 Clinical Trials Experience

Because clinical trials are conducted under widely varying conditions, adverse reaction rates observed in the clinical trials of a drug cannot be directly compared to rates in the clinical trials of another drug and may not reflect the rates observed in practice.

In three double-blind, vehicle-controlled clinical trials (Trial 1, and Trial 2 and Trial 3, which were similarly designed to Trial 1), 1596 adult and pediatric subjects were treated with ZELSUVMI or vehicle gel topically once daily for up to 12 weeks [see Clinical Studies (14)]. In these trials 3% of subjects were less than 2 years of age, and 96% of subjects were 2 to 17 years of age. The trial population included 51% male, 88% White, 6% Black, and 6% Other; for ethnicity, 21% of subjects identified as Hispanic/Latino, 78% as non-Hispanic/Latino, and 1% were not reported. Adverse reactions reported by ≥1% of subjects and more frequently than vehicle-treated subjects are listed in Table 1.

Table 1: Adverse Reactions Reported by ≥ 1% of Subjects with MC Treated with ZELSUVMI (and Greater than Vehicle) Day 1 through Week 12 in Trials 1, 2, and 3
 | ZELSUVMI N=916 |  |  | Vehicle Gel; N=680
Adverse Reaction | Mild n (%) | Moderate n (%) | Severe n (%) | Mild n (%) | Moderate; n (%) | Severe; n (%)
Subjects with any TEAE* | 220 (24.0) | 192 (21.0) | 16 (1.7) | 118 (17.4) | 47 (6.9) | 4 (0.6)
Application Site Pain† | 113 (12.3) | 56 (6.1) | 2 (0.2) | 30 (4.4) | 3 (0.4) | 0
Application Site Erythema | 48 (5.2) | 55 (6.0) | 4 (0.4) | 7 (1.0) | 2 (0.3) | 0
Application Site Pruritus | 36 (3.9) | 15 (1.6) | 1 (0.1) | 5 (0.7) | 2 (0.3) | 0
Application Site Exfoliation | 18 (2.0) | 26 (2.8) | 2 (0.2) | 0 | 0 | 0
Application Site Dermatitis | 16 (1.7) | 26 (2.8) | 3 (0.3) | 3 (0.4) | 2 (0.3) | 0
Application Site Swelling | 17 (1.9) | 14 (1.5) | 1 (0.1) | 3 (0.4) | 1 (0.1) | 0
Pyrexia | 14 (1.5) | 6 (0.7) | 0 | 6 (0.9) | 1 (0.1) | 0
Application Site Erosion | 7 (0.8) | 5 (0.5) | 3 (0.3) | 1 (0.1) | 0 | 0
Application Site Discoloration | 13 (1.4) | 1 (0.1) | 0 | 1 (0.1) | 0 | 0
Application Site Vesicles | 5 (0.5) | 9 (1.0) | 0 | 0 | 1 (0.1) | 0
Vomiting | 5 (0.5) | 7 (0.8) | 0 | 1 (0.1) | 0 | 0
Application Site Irritation | 7 (0.8) | 4 (0.4) | 0 | 0 | 0 | 0
Upper Respiratory Tract Infection | 6 (0.7) | 5 (0.5) | 0 | 4 (0.7) | 1 (0.1) | 0
Application Site Infection | 4 (0.4) | 4 (0.4) | 2 (0.2) | 2 (0.3) | 1 (0.1) | 0
* TEAE – treatment emergent adverse events
† Application site pain also includes application site burning and stinging.

8 USE IN SPECIFIC POPULATIONS

8.1 Pregnancy

Risk Summary

There are no available data on ZELSUVMI use in pregnant women to evaluate for a drug-associated risk of major birth defects, miscarriage or other adverse maternal or fetal outcomes. In animal reproduction studies, oral administration of berdazimer to pregnant rats and rabbits increased malformations in the presence of severe maternal toxicity (see Data). The clinical relevance of this finding is unknown given the bioavailability of berdazimer following oral administration is significantly higher than topical application.

The available data do not allow the calculation of relevant comparisons between the systemic exposure of berdazimer observed in animal studies and the systemic exposure that would be expected in humans after topical use of ZELSUVMI.

The background risk of major birth defects and miscarriage for the indicated population is unknown. All pregnancies have a background risk of birth defect, loss, or other adverse outcomes. In the U.S. general population, the estimated background risk of major birth defects and miscarriage in clinically recognized pregnancies is 2% to 4% and 15% to 20%, respectively.

Data

Animal Data

Systemic embryo-fetal development studies were conducted in rats and rabbits. In an embryo-fetal development study in rats, oral dose levels of 28, 95, or 189 mg/kg/day berdazimer were administered during the period of organogenesis. Maternal mortality and elevated methemoglobin levels were noted in dams receiving doses of 95 and 189 mg/kg/day. The maternal no observable adverse effect level (NOAEL) was 28 mg/kg/day. Fetal skeletal malformations (changes in the lumbar and thoracic centra or arches, missing thoracic arches and centra, additional bone in the thoracic arches, missing lumbar centra and arches, and fused ribs) and visceral malformations (cleft palate) and decreased fetal weights were observed in litters from dams receiving 189 mg/kg/day. The fetal NOAEL was 95 mg/kg/day.

In an embryo-fetal development study in rabbits, oral dose levels of 47, 142, or 284 mg/kg/day berdazimer were administered during the period of organogenesis. Maternal mortality, aborted fetuses, adverse clinical observations, and elevated methemoglobin levels were noted in pregnant rabbits receiving doses of 142 and 284 mg/kg/day. The maternal NOAEL was 47 mg/kg/day. Decreased fetal weights were noted from pregnant rabbits receiving 284 mg/kg/day. The fetal NOAEL was 142 mg/kg/day.

8.2 Lactation

Risk Summary

There are no data on the presence of berdazimer or its metabolite in either human or animal milk, the effects on the breastfed infant, or the effects on milk production. The developmental and health benefits of breastfeeding should be considered along with the mother’s clinical need for ZELSUVMI and any potential adverse effects on the breastfed infant from ZELSUVMI or from the underlying maternal condition.

8.4 Pediatric Use

The safety and effectiveness of ZELSUVMI for the topical treatment of MC have been established in pediatric patients 1 year of age and older. Use of ZELSUVMI for this indication is supported by data from three randomized, vehicle-controlled, double-blind trials involving 1596 subjects of which 1575 were pediatric subjects with MC (904 were exposed to ZELSUVMI; 29 subjects were less than 2 years of age, including one subject less than 1 year of age, and 875 were 2 to 17 years of age) [see Clinical Studies (14)].

The safety and effectiveness of ZELSUVMI have not been established in pediatric patients younger than 1 year of age.

8.5 Geriatric Use

Of the total number of ZELSUVMI-treated subjects in clinical studies for MC, none were 65 to 74 years of age, and one was 75 years of age and older [see Clinical Studies (14)]. Clinical studies of ZELSUVMI did not include sufficient numbers of subjects 65 years of age and older to determine whether they respond differently from younger adult subjects.

11 DESCRIPTION

ZELSUVMI (berdazimer) topical gel, 10.3%, a nitric oxide releasing agent, contains the drug substance berdazimer sodium, a white to off white powder with the chemical name poly[{[3-(methylamino)propyl]silasesquioxane}-co-{[3-(1-methyl-2-nitroso2-oxidohydrazin-1 yl)propyl]silasesquioxane}-co-silicate (1:3:6 x)], partially hydrolyzed (Si : OH ~ 10 : 5), and the following structural and empirical formula:

Structural Formula:

* Denotes shared oxygen atom between bonded constituents; resulting bonds are Si-O-Si or Si‑OH

Empirical formula: [(C4H9N3NaO3.5Si)3(C4H10NO1.5Si)1(SiO2)6(HO0.5)5]0.1n

Due to the insoluble nature of berdazimer sodium, the molecular formula, molecular mass, and average molecular weight range cannot be determined.

ZELSUVMI (berdazimer) topical gel is an opaque white to off-white gel containing 10.3% berdazimer (equivalent to 10.9% berdazimer sodium). ZELSUVMI is supplied as two gel components that are mixed before administration:

- Tube A (14 g): an opaque white to off-white gel containing 240 mg of berdazimer sodium per gram of gel and the inactive ingredients cyclomethicone, hexylene glycol, hydroxypropyl cellulose, and isopropyl alcohol.
- Tube B (17 g): a translucent to opaque white to off-white gel containing the inactive ingredients benzoic acid, carboxymethylcellulose sodium, cyclomethicone, ethanol (13% v/v), glycerin, potassium phosphate monobasic, and purified water.

12 CLINICAL PHARMACOLOGY

12.1 Mechanism of Action

ZELSUVMI is a nitric oxide releasing agent. The mechanism of action for the treatment of molluscum contagiosum is unknown.

12.2 Pharmacodynamics

The pharmacodynamics of ZELSUVMI are unknown.

12.3 Pharmacokinetics

Plasma hydrolyzed MAP3 (hMAP3), a structural marker for berdazimer, and nitrate levels were evaluated in n=34 subjects 2 to 12 years of age with MC. Subjects applied ZELSUVMI once-daily for two weeks to a total treatment area of 484 cm^2 (mean lesion count=34), applying a mean dose of approximately 3 mL/day. No subjects had quantifiable plasma hMAP3 concentrations on day 1; two subjects had quantifiable concentrations on day 15. Mean plasma nitrate levels were similar on days 1 and 15 and remained relatively flat during the PK sampling period (baseline through 1, 3, and 6 hours post-application).

There were no apparent differences in methemoglobin levels throughout the study.

13 NONCLINICAL TOXICOLOGY

13.1 Carcinogenesis, Mutagenesis, Impairment of Fertility

The carcinogenic potential of berdazimer gel was assessed in a 2-year dermal mouse carcinogenicity study. There were no drug-related tumor findings associated with daily topical administration of berdazimer gel to mice at doses up to 4% berdazimer gel.

Berdazimer was mutagenic in a bacterial mutagenicity assay (Ames assay) but was not clastogenic in an in vitro chromosomal aberration assay in human peripheral blood lymphocytes or in an in vivo micronucleus assay in rats.

There were no berdazimer related effects on male or female fertility and early embryonic parameters in rats at oral doses up to 189 mg/kg/day.

14 CLINICAL STUDIES

The efficacy of ZELSUVMI was evaluated in 3 multicenter, randomized, double-blind, parallel-group, vehicle-controlled trials in subjects with MC (Trials 1, 2, and 3; NCT04535531, NCT03927703, and NCT03927716, respectively). Trial 1 enrolled 891 subjects, Trial 2 enrolled 355 subjects, and Trial 3 enrolled 352 subjects. Subjects were randomized 1:1 in Trial 1, and 2:1 in Trials 2 and 3 to receive ZELSUVMI or vehicle applied to MC lesions once daily for up to 12 weeks.

In the three trials, 3% of subjects were less than 2 years of age and 96% of subjects were 2 to 17 years of age. The trial population included 51% male, 88% White, 6% Black, and 6% Other; for ethnicity, 21% of subjects identified as Hispanic/Latino, 78% as non-Hispanic/Latino, and 1% were not reported. Subjects had 3-70 baseline MC lesions. At baseline, the average MC lesion count was 20.2.

The primary efficacy endpoint was the proportion of subjects achieving complete clearance at Week 12. Complete clearance was defined as the subject having a total MC lesion count of 0 at assessment. The key secondary efficacy endpoint was complete clearance rate at Week 8.

Efficacy was demonstrated in Trials 1 and 2. The results are summarized in Table 2.

Table 2: Complete Clearance Rate at Week 12 and Week 8 in Subjects with MC in Trials 1 and 2
 | Trial 1 |  | Trial 2
 | ZELSUVMI; (N=444) | Vehicle; (N=447) | ZELSUVMI; (N=237) | Vehicle; (N=118)
Complete Clearance Rate at Week 12 (Primary Endpoint) | 32.4% | 19.7% | 30.0% | 20.3%
Treatment Difference; (95% Confidence Interval) | 12.8%; (7.1%, 18.6%) |  | 9.2%; (-0.04%, 18.4%)
Complete Clearance Rate at Week 8; (Secondary Endpoint) | 19.6% | 11.6% | 13.9% | 5.9%
Treatment Difference; (95% Confidence Interval) | 7.5%; (3.0%, 12.0%) |  | 7.8%; (1.8%, 13.8%)

In Trial 3, the complete clearance rates at Week 12 were 26% versus 22% for ZELSUVMI and vehicle, respectively, with 95% confidence interval (-5%, 14%).

16 HOW SUPPLIED/STORAGE AND HANDLING

How Supplied

ZELSUVMI (berdazimer) topical gel, 10.3% is supplied in a carton (NDC 83787-103-31) containing:

- Tube A (14 g) with blue label containing berdazimer sodium in an opaque white to off-white gel (NDC 83787-113-14)
- Tube B (17 g) with yellow label containing translucent to opaque white to off-white gel (UPC 83787-0000-17)
- Dosing Guide

Storage and Handling

- Prior to Dispensing: Store ZELSUVMI in a refrigerator between 2°C and 8°C (36°F and 46°F) until dispensed to the patient. Write the “Discard after” date in the space provided on the carton.
- After Dispensing: Store ZELSUVMI at room temperature, between 20°C to 25°C (68°F and 77°F) in a dry location.
- Product contains alcohol and should be kept away from open flame.
- Do not freeze.
- Discard 60 days after removal from refrigeration.

17 PATIENT COUNSELING INFORMATION

Advise the patient or caregiver to read the FDA-approved patient labeling (Patient Information and Instructions for Use).

Application Site Reactions

Advise patients to discontinue ZELSUVMI and seek medical attention immediately if signs or symptoms of application site reactions lasting more than 24 hours occur [see Warnings and Precautions (5.1)].

Administration Instructions

Advise patients that ZELSUVMI is for external use only and is not for ophthalmic, oral, or intravaginal use [see Dosage and Administration (2.2)].

Inform patients that ZELSUVMI is supplied with two gel components that must be mixed together immediately before application. Instruct patients not to premix or store mixed ZELSUVMI [see Dosage and Administration (2.1, 2.2)].

Advise patients to wash hands after applying ZELSUVMI (unless hands are being treated) and avoid transfer of the product to other areas of the skin, including the eye [see Dosage and Administration (2.2)].

Instruct patients to carefully follow the instructions for preparing and administering ZELSUVMI in the ZELSUVMI FDA-approved patient labeling [see Instructions For Use].

Manufactured for:
LNHC, Inc.
Durham, NC 27703

Patient Package Insert

PATIENT INFORMATION

ZELSUVMI™ (zel-SOOV-mee)

(berdazimer) topical gel

Important information: ZELSUVMI is for use on the skin (for topical use) only. Do not use ZELSUVMI near or in your eyes, mouth, or vagina.

What is ZELSUVMI?

ZELSUVMI is a prescription medicine used on the skin (topical) to treat molluscum contagiosum (MC) in adults and children 1 year of age and older.

It is not known if ZELSUVMI is safe and effective in children under 1 year of age.

Before using ZELSUVMI, tell your healthcare provider about all your medical conditions, including if you:

- have other skin problems.
- are pregnant or plan to become pregnant. It is not known if ZELSUVMI will harm your unborn baby.
- are breastfeeding or plan to breastfeed. It is not known if ZELSUVMI passes into your breast milk. Talk to your healthcare provider about the best way to feed your baby during treatment with ZELSUVMI.

Tell your healthcare provider about all the medicines you take, including prescription and over-the-counter medicines, vitamins, and herbal supplements.

How should I use ZELSUVMI?

- Read the Instructions for Use for detailed information about how to properly prepare and apply ZELSUVMI.
- Use ZELSUVMI exactly as your healthcare provider tells you to use it.
- The ZELSUVMI carton contains:
  - 1 tube that contains berdazimer gel (Tube A)
  - 1 tube that contains hydrogel (Tube B)
  - 1 Dosing Guide
- The gels contained in Tube A and Tube B must be mixed together on the Dosing Guide before you apply ZELSUVMI to your skin.
- Do not mix the gels until you are ready to apply ZELSUVMI.
- After mixing, apply an even, thin layer of ZELSUVMI right away to each MC bump.
- Apply ZELSUVMI 1 time each day.
- Do not apply ZELSUVMI near or in your eyes, mouth, vagina, or areas of your skin where you do not have MC.
- Allow ZELSUVMI to dry for 10 minutes and do not swim, take a bath or shower, or wash the areas where you applied ZELSUVMI for 1 hour after you apply it.
- Wash your hands after applying ZELSUVMI, unless your hands are being treated for MC. If someone else applies ZELSUVMI for you, they should wash their hands after applying ZELSUVMI.

What are the possible side effects of ZELSUVMI?
ZELSUVMI may cause serious side effects, including:

- Application site reactions. Application site reactions, including allergic skin reactions, are common where ZELSUVMI is applied to your skin, but can also be severe. Stop using ZELSUVMI and tell your healthcare provider right away if you develop pain, burning, stinging, itching, swelling, or redness of your skin that lasts for more than 24 hours after treatment with ZELSUVMI.

The most common side effects of ZELSUVMI include:

- the following skin side effects at the application site:
  - pain
  - burning
  - stinging
  - redness
  - itching
  - peeling or flaking
  - itchy, dry skin rash

- swelling
- breakdown of the outer layer of the skin (erosion)
- lightening or darkening of the skin
- blisters
- irritation
- infection

These are not all of the possible side effects of ZELSUVMI.

Call your doctor for medical advice about side effects. You may report side effects to FDA at 1-800-FDA-1088.

How should I store ZELSUVMI?

- Store ZELSUVMI at room temperature between 68°F to 77°F (20°C to 25°C) in a dry location.
- Do not premix or store mixed ZELSUVMI.
- Product contains alcohol and should be kept away from open flame.
- Do not freeze ZELSUVMI.
- After use, immediately put caps back on Tube A (berdazimer gel) and Tube B (hydrogel) tightly.
- Throw away if not used within 60 days after receiving ZELSUVMI.

Keep ZELSUVMI and all medicines out of the reach of children.

General information about the safe and effective use of ZELSUVMI.

Medicines are sometimes prescribed for purposes other than those listed in a Patient Information leaflet. Do not use ZELSUVMI for a condition for which it was not prescribed. Do not give ZELSUVMI to other people, even if they have the same symptoms that you have. It may harm them. You can ask your pharmacist or healthcare provider for information about ZELSUVMI that is written for health professionals.

What are the ingredients in ZELSUVMI?

Tube A

Active ingredient: berdazimer sodium

Inactive ingredients: cyclomethicone, hexylene glycol, hydroxypropyl cellulose, and isopropyl alcohol

Tube B

Inactive ingredients: benzoic acid, carboxymethylcellulose sodium, cyclomethicone, ethanol, glycerin, potassium phosphate monobasic, and purified water

Manufactured for: LNHC, Inc.

Durham, NC 27703

U.S. Patents: www.pelthos.com/patents

For more information, call 1-855-330-7546 or go to www.Zelsuvmi.com.

This Patient Information has been approved by the U.S. Food and Drug Administration. Issued: 01/2024